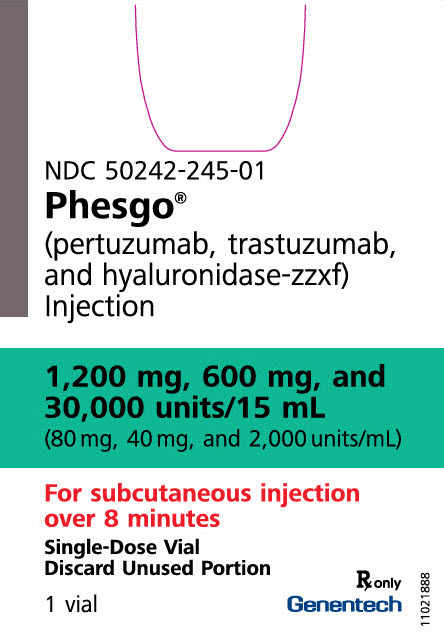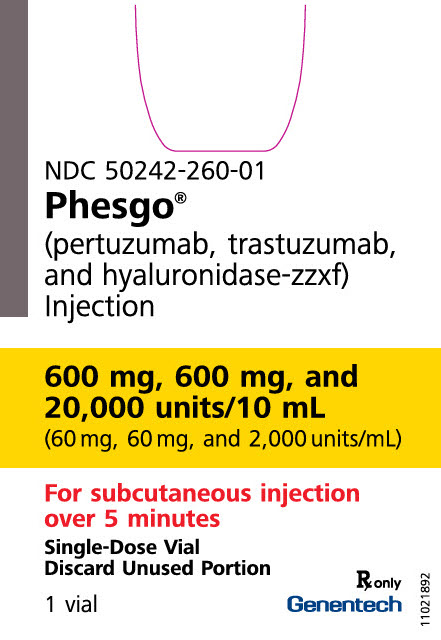 DRUG LABEL: Phesgo
NDC: 50242-245 | Form: INJECTION, SOLUTION
Manufacturer: Genentech, Inc.
Category: prescription | Type: HUMAN PRESCRIPTION DRUG LABEL
Date: 20251205

ACTIVE INGREDIENTS: PERTUZUMAB 1200 mg/15 mL; TRASTUZUMAB 600 mg/15 mL; HYALURONIDASE (HUMAN RECOMBINANT) 30000 U/15 mL
INACTIVE INGREDIENTS: HISTIDINE; HISTIDINE HYDROCHLORIDE; TREHALOSE DIHYDRATE; SUCROSE; POLYSORBATE 20; METHIONINE; WATER

HIGHLIGHTS OF PRESCRIBING INFORMATION

These highlights do not include all the information needed to use PHESGO safely and effectively. See full prescribing information for PHESGO.
PHESGO® (pertuzumab, trastuzumab, and hyaluronidase-zzxf) injection, for subcutaneous use
Initial U.S. Approval: 2020

WARNING: CARDIOMYOPATHY, EMBRYO-FETAL TOXICITY, and PULMONARY TOXICITY

See full prescribing information for complete boxed warning.

Cardiomyopathy: PHESGO administration can result in subclinical and clinical cardiac failure manifesting as CHF, and decreased LVEF, with greatest risk when administered concurrently with anthracyclines. Evaluate cardiac function prior to and during treatment. Discontinue PHESGO for cardiomyopathy. (2.3, 5.1)

Embryo-fetal Toxicity: Exposure to PHESGO can result in embryo-fetal death and birth defects. Advise patients of these risks and the need for effective contraception. (5.2, 8.1, 8.3)

Pulmonary Toxicity: Discontinue PHESGO for anaphylaxis, angioedema, interstitial pneumonitis, or acute respiratory distress syndrome. (5.3)

1 INDICATIONS AND USAGE

PHESGO is a combination of pertuzumab and trastuzumab, HER2/neu receptor antagonists, and hyaluronidase, an endoglycosidase, indicated for:

- Use in combination with chemotherapy as:
  - neoadjuvant treatment of patients with HER2-positive, locally advanced, inflammatory, or early stage breast cancer (either greater than 2 cm in diameter or node positive) as part of a complete treatment regimen for early breast cancer. (1.1)
  - adjuvant treatment of patients with HER2-positive early breast cancer at high risk of recurrence (1.1)
- Use in combination with docetaxel for treatment of patients with HER2-positive metastatic breast cancer (MBC) who have not received prior anti-HER2 therapy or chemotherapy for metastatic disease. (1.2)

2 DOSAGE AND ADMINISTRATION

- For subcutaneous use in the thigh only. (2.2)
- PHESGO has different dosage and administration instructions than intravenous pertuzumab and trastuzumab products. (2.2)
- Do not administer intravenously. (2.2)
- Perform HER2 testing using FDA-approved tests by laboratories with demonstrated proficiency. (1, 2.1)
- The initial dose of PHESGO is 1,200 mg pertuzumab, 600 mg trastuzumab, and 30,000 units hyaluronidase administered subcutaneously over approximately 8 minutes, followed every 3 weeks by a dose of 600 mg pertuzumab, 600 mg trastuzumab, and 20,000 units hyaluronidase administered subcutaneously over approximately 5 minutes. (2.2)
- Neoadjuvant: administer PHESGO by subcutaneous injection every 3 weeks and chemotherapy by intravenous infusion preoperatively for 3 to 6 cycles. (2.2)
- Adjuvant: administer PHESGO by subcutaneous injection every 3 weeks and chemotherapy by intravenous infusion postoperatively for a total of 1 year (up to 18 cycles). (2.2)
- MBC: administer PHESGO by subcutaneous injection and docetaxel by intravenous infusion every 3 weeks. (2.2)

3 DOSAGE FORMS AND STRENGTHS

Injection:

- 1,200 mg pertuzumab, 600 mg trastuzumab, and 30,000 units hyaluronidase/15 mL (80 mg, 40 mg, and 2,000 units/mL) of solution in a single-dose vial. (3)
- 600 mg pertuzumab, 600 mg trastuzumab, and 20,000 units hyaluronidase/10 mL (60 mg, 60 mg, and 2,000 units/mL) of solution in a single-dose vial. (3)

4 CONTRAINDICATIONS

PHESGO is contraindicated in patients with known hypersensitivity to pertuzumab, or trastuzumab, or hyaluronidase, or to any of its excipients. (4)

5 WARNINGS AND PRECAUTIONS

- Exacerbation of Chemotherapy-Induced Neutropenia. (5.4)
- Hypersensitivity and Administration-Related Reactions (ARRs): Monitor patients for systemic hypersensitivity reactions. Permanently discontinue PHESGO in patients who experience anaphylaxis or severe hypersensitivity reactions. (5.5)

6 ADVERSE REACTIONS

Neoadjuvant and Adjuvant Treatment of Breast Cancer

- The most common adverse reactions (>30%) with PHESGO were alopecia, nausea, diarrhea, anemia, and asthenia. (6.1)

Metastatic Breast Cancer (based on intravenous pertuzumab)

- The most common adverse reactions (> 30%) with pertuzumab in combination with trastuzumab and docetaxel were diarrhea, alopecia, neutropenia, nausea, fatigue, rash, and peripheral neuropathy. (6.1)

To report SUSPECTED ADVERSE REACTIONS, contact Genentech at 1-888-835-2555 or FDA at 1-800-FDA-1088 or www.fda.gov/medwatch.

8 USE IN SPECIFIC POPULATIONS

Females and Males of Reproductive Potential: Verify the pregnancy status of females prior to initiation of PHESGO. (8.3)

FULL PRESCRIBING INFORMATION

WARNING: CARDIOMYOPATHY, EMBRYO-FETAL TOXICITY, and PULMONARY TOXICITY

Cardiomyopathy

PHESGO administration can result in subclinical and clinical cardiac failure. The incidence and severity were highest in patients receiving PHESGO with anthracycline-containing chemotherapy regimens. Evaluate cardiac function prior to and during treatment with PHESGO. Discontinue PHESGO treatment in patients receiving adjuvant therapy and withhold PHESGO in patients with metastatic disease for clinically significant decrease in left ventricular function [see Dosage and Administration (2.3) and Warnings and Precautions (5.1)].

Embryo-fetal Toxicity

Exposure to PHESGO can result in embryo-fetal death and birth defects, including oligohydramnios and oligohydramnios sequence manifesting as pulmonary hypoplasia, skeletal abnormalities, and neonatal death. Advise patients of these risks and the need for effective contraception [see Warnings and Precautions (5.2) and Use in Specific Populations (8.1), (8.3)].

Pulmonary Toxicity

PHESGO administration can result in serious and fatal pulmonary toxicity. Discontinue PHESGO for anaphylaxis, angioedema, interstitial pneumonitis, or acute respiratory distress syndrome. Monitor patients until symptoms completely resolve [see Warnings and Precautions (5.3)].

1 INDICATIONS AND USAGE

1.1 Early Breast Cancer (EBC)

PHESGO is indicated for use in combination with chemotherapy for

- the neoadjuvant treatment of adult patients with HER2-positive, locally advanced, inflammatory, or early stage breast cancer (either greater than 2 cm in diameter or node positive) as part of a complete treatment regimen for early breast cancer [see Dosage and Administration (2.2) and Clinical Studies (14.2)].
- the adjuvant treatment of adult patients with HER2-positive early breast cancer at high risk of recurrence [see Dosage and Administration (2.2) and Clinical Studies (14.2)].

Select patients for therapy based on an FDA-approved companion diagnostic test [see Dosage and Administration (2.1)].

1.2 Metastatic Breast Cancer (MBC)

PHESGO is indicated for use in combination with docetaxel for the treatment of adult patients with HER2-positive metastatic breast cancer who have not received prior anti-HER2 therapy or chemotherapy for metastatic disease [see Dosage and Administration (2.2) and Clinical Studies (14.1)].

Select patients for therapy based on an FDA-approved companion diagnostic test [see Dosage and Administration (2.1)].

2 DOSAGE AND ADMINISTRATION

2.1 Patient Selection

Select patients based on HER2 protein overexpression or HER2 gene amplification in tumor specimens [see Indications and Usage (1) and Clinical Studies (14)]. Assessment of HER2 protein overexpression and HER2 gene amplification should be performed using FDA-approved tests specific for breast cancer by laboratories with demonstrated proficiency. Information on the FDA-approved tests for the detection of HER2 protein overexpression and HER2 gene amplification is available at: http://www.fda.gov/CompanionDiagnostics.

Improper assay performance, including use of suboptimally fixed tissue, failure to utilize specified reagents, deviation from specific assay instructions, and failure to include appropriate controls for assay validation, can lead to unreliable results.

2.2 Important Dosage and Administration Information

PHESGO is for subcutaneous use only in the thigh. Do not administer intravenously.

PHESGO has different dosage and administration instructions than intravenous pertuzumab, intravenous trastuzumab, and subcutaneous trastuzumab when administered alone.

Do not substitute PHESGO for or with pertuzumab, trastuzumab, ado-trastuzumab emtansine, or fam-trastuzumab deruxtecan.

PHESGO must always be administered by a healthcare professional.

In patients receiving an anthracycline-based regimen for early breast cancer, administer PHESGO following completion of the anthracycline.

In patients receiving PHESGO for early breast cancer with docetaxel or paclitaxel, administer docetaxel or paclitaxel after PHESGO.

In patients receiving PHESGO for metastatic breast cancer with docetaxel, administer docetaxel after PHESGO.

Observe patients for a minimum of 30 minutes after initial dose of PHESGO and 15 minutes after each maintenance dose of PHESGO for signs or hypersensitivity symptoms or administration-related reactions. Medications to treat such reactions, as well as emergency equipment, should be available for immediate use [see Warnings and Precautions (5.5)].

2.3 Recommended Doses and Schedules

The recommended dosage and administration schedule for PHESGO are shown in Table 1.

Table 1: Recommended Dosage and Administration Schedule
Dose | Strength | Administration Instructions
Initial dose | 1,200 mg pertuzumab, 600 mg trastuzumab, and 30,000 units hyaluronidase in 15 mL | Administer subcutaneously over approximately 8 minutes
 | (1,200 mg, 600 mg, and 30,000 units/15 mL)
Maintenance dose (administer every 3 weeks) | 600 mg pertuzumab, 600 mg trastuzumab, and 20,000 units hyaluronidase in 10 mL (600 mg, 600 mg, and 20,000 units/10 mL) | Administer subcutaneously over approximately 5 minutes every 3 weeks

No dose adjustments for PHESGO are required for patient body weight or for concomitant chemotherapy regimen.

Patients currently receiving intravenous pertuzumab and trastuzumab can transition to PHESGO. In patients receiving intravenous pertuzumab and trastuzumab with < 6 weeks since their last dose, administer PHESGO as a maintenance dose of 600 mg pertuzumab/600 mg trastuzumab and every 3 weeks for subsequent administrations. In patients receiving intravenous pertuzumab and trastuzumab with ≥ 6 weeks since their last dose, administer PHESGO as an initial dose of 1,200 mg pertuzumab/600 mg trastuzumab, followed by a maintenance dose of 600 mg pertuzumab/600 mg trastuzumab every 3 weeks for subsequent administrations.

Neoadjuvant Treatment of Breast Cancer

Administer PHESGO every 3 weeks for 3 to 6 cycles as part of a treatment regimen for early breast cancer [see Clinical Studies (14.2)].

Refer to the prescribing information for pertuzumab, administered in combination with trastuzumab and chemotherapy, for recommended dose and dosage modifications.

Following surgery, patients should continue to receive PHESGO to complete 1 year of treatment (up to 18 cycles) or until disease recurrence or unmanageable toxicity, whichever occurs first, as a part of a complete regimen for early breast cancer.

Adjuvant Treatment of Breast Cancer

Administer PHESGO every 3 weeks for a total of 1 year (up to 18 cycles) or until disease recurrence or unmanageable toxicity, whichever occurs first, as part of a complete regimen for early breast cancer, including standard anthracycline- and/or taxane-based chemotherapy. Start PHESGO on Day 1 of the first taxane-containing cycle [see Clinical Studies (14.2)].

Metastatic Breast Cancer (MBC)

When administered with PHESGO, the recommended initial dose of docetaxel is 75 mg/m^2 administered as an intravenous infusion. The dose may be escalated to 100 mg/m^2 administered every 3 weeks if the initial dose is well tolerated. Administer PHESGO until disease progression or unmanageable toxicity, whichever occurs first.

2.4 Dose Modification

Dose Modification for Delayed or Missed Doses

For delayed or missed doses of PHESGO, if the time between two sequential injections is less than 6 weeks, administer the maintenance dose of 600 mg, 600 mg, and 20,000 units/10 mL. Do not wait until the next planned dose.

If the time between two sequential injections is 6 weeks or more, re-administer the initial dose of 1,200 mg, 600 mg, and 30,000 units/15 mL, followed every 3 weeks thereafter by a maintenance dose of 600 mg, 600 mg, and 20,000 units/10 mL.

For chemotherapy dose modifications, see relevant prescribing information.

Cardiomyopathy [see Boxed Warning, Warnings and Precautions (5.1)]

Assess left ventricular ejection fraction (LVEF) prior to initiation of PHESGO and at regular intervals during treatment as indicated in Table 2.

The recommendations on dose modifications in the event of LVEF dysfunction are indicated in Table 2 [see Warnings and Precautions (5.1)].

Table 2: Dose Modifications for Left Ventricular Dysfunction
 | Pre-treatment LVEF: | Monitor LVEF every: | Withhold PHESGO for at least 3 weeks for an LVEF decrease to: |  | Resume PHESGO after 3 weeks if LVEF has recovered to:
Early Breast Cancer | ≥ 55% [For patients receiving anthracycline-based chemotherapy, a LVEF of ≥ 50% is required after completion of anthracyclines, before starting PHESGO] | ~12 weeks (once during neoadjuvant therapy) | <50% with a fall of ≥10%-points below pre-treatment value |  | Either
Early Breast Cancer | ≥ 55% [For patients receiving anthracycline-based chemotherapy, a LVEF of ≥ 50% is required after completion of anthracyclines, before starting PHESGO] | ~12 weeks (once during neoadjuvant therapy) | <50% with a fall of ≥10%-points below pre-treatment value |  | ≥50% | <10% points below pre-treatment value
Metastatic Breast Cancer | ≥ 50% | ~12 weeks | Either |  | Either
Metastatic Breast Cancer | ≥ 50% | ~12 weeks | <40% | 40%-45% with a fall of ≥10%-points below pre-treatment value | >45% | 40%-45% with a fall of <10%-points below pre-treatment value

If after a repeat assessment within approximately 3 weeks, the LVEF has not improved, has declined further, and/or the patient is symptomatic, permanently discontinue PHESGO [see Warnings and Precautions (5.1)].

Hypersensitivity and Administration-Related Reactions

Discontinue the injection immediately if the patient experiences a serious hypersensitivity reaction (e.g. anaphylaxis) [see Warnings and Precautions (5.5)].

2.5 Preparation for Administration

To prevent medication errors, it is important to check the vial labels to ensure that the drug being prepared and administered is PHESGO and not intravenous pertuzumab, or intravenous trastuzumab, or subcutaneous trastuzumab.

Parenteral drug products should be inspected visually for particulate matter and discoloration prior to administration, whenever solution and container permit. Do not use vial if particulates or discoloration is present. Do not shake. Discard any unused portion remaining in the vial.

For both the initial and maintenance dose, each corresponding PHESGO vial is ready-to-use for one subcutaneous injection and should not be diluted.

A syringe, a transfer needle, and an injection needle are needed to withdraw PHESGO solution from the vial and inject it subcutaneously. PHESGO may be injected using 25G-27G (3/8"-5/8") hypodermic injection needles.

To avoid needle clogging, attach the hypodermic injection needle to the syringe immediately prior to administration followed by volume adjustment to 15 mL (initial dose) and 10 mL (maintenance dose). If the dose is not to be administered immediately, and the solution of PHESGO has been withdrawn from the vial into the syringe, replace the transfer needle with a syringe closing cap. Label the syringe with the peel-off sticker and store the syringe in the refrigerator [2°C to 8°C (36°F to 46°F)] for up to 24 hours and at room temperature [20°C to 25°C (68°F to 77°F)] for up to 4 hours and avoid unnecessary storage.

PHESGO is compatible with stainless steel, polypropylene, polycarbonate, polyethylene, polyurethane, polyvinyl chloride and fluorinated ethylene polypropylene.

Administration

- Administer PHESGO 1,200 mg, 600 mg, 30,000 units/15 mL subcutaneously over approximately 8 minutes
- Administer PHESGO 600 mg, 600 mg, 20,000 units/10 mL subcutaneously over approximately 5 minutes

The subcutaneous injection site should be alternated between the left and right thigh only. New injections should be given at least 1 inch (2.5 cm) from the previous site on healthy skin and never into areas where the skin is red, bruised, tender, or hard. Do not split the dose between two syringes or between two sites of administration. During the treatment course with PHESGO, other medications for subcutaneous administration should preferably be injected at different sites.

3 DOSAGE FORMS AND STRENGTHS

Injection: PHESGO is a clear to opalescent, and colorless to slightly brownish solution provided as:

- 1,200 mg pertuzumab, 600 mg trastuzumab, and 30,000 units hyaluronidase/15 mL (80 mg, 40 mg, and 2,000 units/mL) of solution in a single-dose vial
- 600 mg pertuzumab, 600 mg trastuzumab, and 20,000 units hyaluronidase/10 mL (60 mg, 60 mg, and 2,000 units/mL) of solution in a single-dose vial

4 CONTRAINDICATIONS

PHESGO is contraindicated in patients with known hypersensitivity to pertuzumab, or trastuzumab, or hyaluronidase, or to any of its excipients.

5 WARNINGS AND PRECAUTIONS

5.1 Cardiomyopathy

PHESGO can cause hypertension, arrhythmias, left ventricular cardiac dysfunction, disabling cardiac failure, cardiomyopathy, and cardiac death [see Boxed Warning: Cardiomyopathy]. PHESGO can cause asymptomatic decline in LVEF.

An increased incidence of LVEF decline has been observed in patients treated with intravenous pertuzumab, intravenous trastuzumab, and docetaxel. A 4-6 fold increase in the incidence of symptomatic myocardial dysfunction has been reported among patients receiving trastuzumab, with the highest absolute incidence occurring when trastuzumab was administered with an anthracycline.

Patients who receive anthracycline after stopping PHESGO may also be at increased risk of cardiac dysfunction [see Drug Interactions (7) and Clinical Pharmacology (12.2)].

Cardiac Monitoring

Prior to initiation of PHESGO, conduct a thorough cardiac assessment, including history, physical examination, and determination of LVEF by echocardiogram or MUGA scan.

During treatment with PHESGO, assess LVEF at regular intervals [see Dosage and Administration (2.4)].

If after a repeat assessment within approximately 3 weeks, the LVEF has not improved, has declined further, and/or the patient is symptomatic, permanently discontinue PHESGO.

Following completion of PHESGO, continue to monitor for cardiomyopathy and assess LVEF measurements every 6 months for at least 2 years as a component of adjuvant therapy.

PHESGO

In the FeDeriCa trial, the percentage of patients with at least one cardiac disorder was 22% in the PHESGO arm. The most frequent cardiac adverse reaction in the PHESGO arm was ejection fraction decreased.

The incidence of cardiac failure (NYHA Class III/IV) with a LVEF decline ≥ 10% and a drop to less than 50% was 0.8% in the PHESGO arm. Confirmed asymptomatic or mildly symptomatic (NYHA Class II) declines in LVEF ≥ 10% and a drop to less than 50% was 1.2% in the PHESGO arm [see Adverse Reactions (6.1)].

PHESGO and/or intravenous pertuzumab and trastuzumab have not been studied in patients with a pretreatment LVEF value of < 55% (EBC) or <50% (MBC); a prior history of CHF, conditions that could impair left ventricular function such as uncontrolled hypertension, recent myocardial infarction, serious cardiac arrhythmia requiring treatment or a cumulative prior anthracycline exposure to > 360 mg/m^2 of doxorubicin or its equivalent.

5.2 Embryo-Fetal Toxicity

PHESGO can cause fetal harm when administered to a pregnant woman. In post-marketing reports, use of intravenous trastuzumab during pregnancy resulted in cases of oligohydramnios and oligohydramnios sequence manifesting as pulmonary hypoplasia, skeletal abnormalities, and neonatal death. In an animal reproduction study, administration of intravenous pertuzumab to pregnant cynomolgus monkeys during the period of organogenesis resulted in oligohydramnios, delayed fetal kidney development, and embryo-fetal death at exposures 2.5 to 20 times the exposure in humans at the recommended dose, based on Cmax.

Verify the pregnancy status of females of reproductive potential prior to the initiation of PHESGO. Advise pregnant women and females of reproductive potential that exposure to PHESGO during pregnancy or within 7 months prior to conception can result in fetal harm. Advise females of reproductive potential to use effective contraception during treatment and for 7 months following the last dose of PHESGO [see Use in Specific Populations (8.1, 8.3) and Clinical Pharmacology (12.3)].

5.3 Pulmonary Toxicity

PHESGO can cause serious and fatal pulmonary toxicity. These adverse reactions have been reported with intravenous trastuzumab. Pulmonary toxicity includes dyspnea, interstitial pneumonitis, pulmonary infiltrates, pleural effusions, non-cardiogenic pulmonary edema, pulmonary insufficiency and hypoxia, acute respiratory distress syndrome, and pulmonary fibrosis. Patients with symptomatic intrinsic lung disease or with extensive tumor involvement of the lungs, resulting in dyspnea at rest, appear to have more severe toxicity.

5.4 Exacerbation of Chemotherapy-Induced Neutropenia

PHESGO may exacerbate chemotherapy-induced neutropenia. In randomized controlled clinical trials with intravenous trastuzumab, Grade 3-4 neutropenia and febrile neutropenia were higher in patients receiving trastuzumab in combination with myelosuppressive chemotherapy as compared to those who received chemotherapy alone. The incidence of septic death was similar among patients who received trastuzumab and those who did not.

5.5 Hypersensitivity and Administration-Related Reactions

Severe administration-related reactions (ARRs), including hypersensitivity, anaphylaxis, and events with fatal outcomes, have been associated with intravenous pertuzumab and trastuzumab. Patients experiencing dyspnea at rest due to complications of advanced malignancy and comorbidities may be at increased risk of a severe or of a fatal ARR.

In the FeDeriCa trial, the incidence of hypersensitivity was 1.2% in the PHESGO arm. Administration-related reactions occurred in 21% of patients who received PHESGO. In the PHESGO arm, the most common administration-related reactions were injection site reaction (15%) and injection site pain (2%).

Closely monitor patients during and for 30 minutes after the injection of initial dose and during and for 15 minutes following subsequent injections of maintenance dose of PHESGO. If a significant injection-related reaction occurs, slow down or pause the injection and administer appropriate medical therapies. Evaluate and carefully monitor patients until complete resolution of signs and symptoms.

Permanently discontinue with PHESGO in patients who experience anaphylaxis or severe injection-related reactions. Medications to treat such reactions, as well as emergency equipment, should be available for immediate use. For patients experiencing reversible Grade 1 or 2 hypersensitivity reactions, consider pre-medication with an analgesic, antipyretic, or an antihistamine prior to readministration of PHESGO [see Adverse Reactions (6.1)].

PHESGO is contraindicated in patients with known hypersensitivity to pertuzumab, trastuzumab, hyaluronidase or to any of its excipients [see Contraindications (4)].

6 ADVERSE REACTIONS

The following adverse reactions are discussed in greater detail in other sections of the label:

- Cardiomyopathy [see Warnings and Precautions (5.1)]
- Embryo-Fetal Toxicity [see Warnings and Precautions (5.2)]
- Pulmonary Toxicity [see Warnings and Precautions (5.3)]
- Exacerbation of Chemotherapy-Induced Neutropenia [see Warnings and Precautions (5.4)]
- Hypersensitivity and Administration-Related Reactions [see Warnings and Precautions (5.5)]

6.1 Clinical Trials Experience

Because clinical trials are conducted under widely varying conditions, adverse reaction rates observed in the clinical trials of a drug cannot be directly compared to rates in the clinical trials of another drug and may not reflect the rates observed in practice.

Neoadjuvant and Adjuvant Treatment of Breast Cancer

The safety of PHESGO was evaluated in an open-label, multicenter, randomized trial (FeDeriCa) conducted in 500 patients with HER2 overexpressing early breast cancer [see Clinical Studies (14.2)].

Patients were randomized to receive either PHESGO (1,200 mg pertuzumab, 600 mg trastuzumab, and 30,000 units hyaluronidase/15 mL) followed every 3 weeks by a maintenance dose of 600 mg pertuzumab, 600 mg trastuzumab, and 20,000 units hyaluronidase/10 mL or the recommended dosages for intravenous pertuzumab and intravenous trastuzumab. Patients were randomized to receive 8 cycles of neoadjuvant chemotherapy with concurrent administration of 4 cycles of either PHESGO or intravenous pertuzumab and trastuzumab during cycles 5-8, followed by surgery. Following surgery, patients continued therapy with PHESGO alone or intravenous pertuzumab and trastuzumab (intravenous or subcutaneously administered) as treated prior to surgery, for an additional 14 cycles, to complete 18 cycles. The median duration of treatment for PHESGO was 24 weeks (range: 0-42 weeks).

Serious adverse reactions occurred in 16% of patients who received PHESGO. Serious adverse reactions in > 1% of patients included febrile neutropenia (4%), neutropenic sepsis (1%), and neutrophil count decreased (1%). One fatal adverse reaction occurred in 1/248 (0.4%) of patients, which was due to acute myocardial infarction, and occurred prior to the start of HER2 targeted treatment with PHESGO.

Adverse reactions resulting in permanent discontinuation of any study drug occurred in 8% of patients on the PHESGO arm. Adverse reactions which resulted in permanent discontinuation of PHESGO were ejection fraction decreased (1.2%), cardiac failure (0.8%), and pneumonitis/pulmonary fibrosis (0.8%).

Dosage interruptions due to an adverse reaction occurred in 40% of patients who received PHESGO. Adverse reactions which required dosage interruption in > 1% of patients who received PHESGO included neutropenia (8%), neutrophil count decreased (4%), and diarrhea (7%).

Table 3 summarizes the adverse reactions in FeDeriCa.

Table 3: Adverse Reactions (≥5%) in Patients Who Received PHESGO in FeDeriCa
Adverse Reactions | PHESGO (n=248) |  | Intravenous pertuzumab plus intravenous or subcutaneous trastuzumab (n=252)
 | All Grades % | Grades 3 – 4 % | All Grades % | Grades 3 – 4 %
Skin and subcutaneous tissue disorders
Alopecia | 77 | 0 | 71 | 0.4
Dry skin | 15 | 0.4 | 13 | 0
Rash | 16 | 0.4 | 21 | 0
Nail discoloration | 9 | 0 | 6 | 0
Erythema | 9 | 0 | 5 | 0
Dermatitis | 7 | 0 | 6 | 0
Nail disorder | 7 | 0 | 7 | 0.4
Palmar-plantar erythrodysaesthesia syndrome | 6 | 0.8 | 5 | 0.4
Gastrointestinal disorders
Nausea | 60 | 2 | 61 | 1.6
Diarrhea | 60 | 7 | 57 | 4.8
Stomatitis | 25 | 0.8 | 24 | 0.8
Constipation | 22 | 0 | 21 | 0
Vomiting | 20 | 0.8 | 19 | 1.2
Dyspepsia | 14 | 0 | 12 | 0
Hemorrhoids | 9 | 0 | 4.0 | 0
Abdominal pain upper | 8 | 0 | 6 | 0
Abdominal pain | 9 | 0.4 | 6 | 0
Blood and lymphatic system disorders
Anemia | 36 | 1.6 | 43 | 4.4
Neutropenia | 22 | 14 | 27 | 14
Leukopenia | 9 | 2.4 | 14 | 2
Febrile neutropenia | 7 | 7 | 6 | 6
General disorders and administration site conditions
Asthenia | 31 | 0.4 | 32 | 2.4
Fatigue | 29 | 2 | 24 | 2
Mucosal inflammation | 15 | 0.8 | 20 | 1.2
Injection site reaction | 15 | 0 | 0.8 | 0
Pyrexia | 13 | 0 | 16 | 0.4
Edema peripheral | 8 | 0 | 10 | 0
Malaise | 7 | 0 | 6 | 0.4
Influenza-like illness | 5 | 0 | 3.6 | 0
Nervous system disorders
Dysgeusia | 17 | 0 | 14 | 0
Peripheral sensory neuropathy | 16 | 0.8 | 14 | 0.4
Headache | 17 | 0 | 25 | 0.8
Neuropathy peripheral | 12 | 0.4 | 15 | 2
Paresthesia | 10 | 0.8 | 8 | 0
Dizziness | 13 | 0 | 11 | 0
Investigations
Weight decreased | 11 | 0.8 | 6 | 0.8
Musculoskeletal and connective tissue disorders
Myalgia | 25 | 0.4 | 19 | 0.4
Arthralgia | 24 | 0 | 28 | 0.4
Back pain | 10 | 0 | 4.8 | 0
Bone pain | 7 | 0 | 5 | 0
Pain in extremity | 6 | 0 | 8 | 0
Muscle spasms | 6 | 0 | 7 | 0
Musculoskeletal pain | 6 | 0.4 | 8 | 0
Respiratory, thoracic and mediastinal disorder
Cough | 15 | 0.4 | 13 | 0
Epistaxis | 12 | 0 | 14 | 0.4
Dyspnea | 10 | 1.2 | 5 | 0
Rhinorrhea | 7 | 0 | 4.4 | 0
Infections and infestations
Upper respiratory tract infection | 11 | 0 | 8 | 0.8
Nasopharyngitis | 9 | 0 | 10 | 0
Paronychia | 7 | 0.4 | 3.6 | 0
Urinary tract infection | 7 | 0.4 | 5 | 0
Injury, poisoning and procedural complications
Procedural pain | 13 | 0 | 10 | 0
Radiation skin injury | 19 | 0.4 | 19 | 0.4
Infusion related reaction | 3.6 | 0 | 15 | 0.8
Metabolism and nutrition disorders
Decreased appetite | 17 | 0.8 | 19 | 0.4
Hypokalemia | 7 | 1.6 | 8 | 0
Psychiatric disorders
Insomnia | 17 | 0 | 13 | 0.4
Eye disorders
Lacrimation increased | 5 | 0.4 | 6 | 0
Dry eye | 5 | 0.4 | 3.2 | 0
Vascular disorders
Hot flush | 12 | 0 | 13 | 0

Clinically relevant adverse reactions in <5% of patients who received PHESGO include ejection fraction decreased (3.6%) and pruritus (3.2%).

In the FeDeriCa trial, when PHESGO was administered alone, adverse reactions occurred in <10% of patients with the exception of radiation skin injury (20%), arthralgia (19%), diarrhea (17%), injection site reaction (13%), dyspepsia (12%), asthenia (11%), hot flush (11%), and pruritus (10%).

Table 4 summarizes the laboratory abnormalities in FeDeriCa.

Table 4: Select Laboratory Abnormalities (≥5%) that Worsened from Baseline in Patients Who Received PHESGO in FeDeriCa [The denominator used to calculate the rate varied from 163 to 252 based on the number of patients with a baseline value and at least one post-treatment value.]
Laboratory Abnormality | PHESGO (n=248) |  | Intravenous pertuzumab plus intravenous or subcutaneous trastuzumab (n=252)
Laboratory Abnormality | All Grades % | Grades 3 – 4 % | All Grades % | Grades 3 – 4 %
Hematology
Hemoglobin (low) | 90 | 2.8 | 92 | 4.4
Lymphocytes, Absolute (low) | 89 | 37 | 88 | 36
Total Leukocyte Count (low) | 82 | 25 | 78 | 25
Neutrophils, Total Absolute (low) | 68 | 30 | 67 | 33
Platelet (low) | 27 | 0 | 28 | 0.4
Chemistry
Creatinine (high) | 84 | 0 | 87 | 0.4
Alanine aminotransferase (high) | 58 | 1.6 | 68 | 2.4
Aspartate aminotransferase (high) | 50 | 0.8 | 58 | 0.8
Potassium (low) | 17 | 5.2 | 17 | 2.8
Albumin (low) | 16 | 0 | 20 | 0.4
Potassium (high) | 13 | 1.2 | 9 | 0
Sodium (low) | 13 | 0.4 | 10 | 1.6
Bilirubin (high) | 9 | 0 | 9 | 0.4
Glucose (low) | 9 | 0 | 9 | 0.4
Sodium (high) | 7 | 0.8 | 10 | 0.8

Other Clinical Trials Experience

The safety of the addition of intravenous pertuzumab to trastuzumab in combination with chemotherapy has been established in studies conducted in patients with HER2 overexpressing early breast cancer. The following adverse reactions have been reported following administration of intravenous pertuzumab and trastuzumab: diarrhea, alopecia, nausea, fatigue, neutropenia, vomiting, peripheral neuropathy, constipation, anemia, asthenia, mucosal inflammation, myalgia, and thrombocytopenia. Refer to the Prescribing Information for pertuzumab for more information.

The safety of intravenous pertuzumab, trastuzumab and docetaxel has been established in patients with HER2 overexpressing metastatic breast cancer. The following adverse reactions have been reported following administration of intravenous pertuzumab and trastuzumab: diarrhea, alopecia, neutropenia, nausea, fatigue, rash, and peripheral neuropathy. Refer to the Prescribing Information for pertuzumab for more information.

6.2 Postmarketing Experience

The following adverse reactions have been identified with the use of intravenous pertuzumab and trastuzumab. Because these reactions are reported voluntarily from a population of uncertain size, it is not always possible to reliably estimate their frequency or establish a causal relationship to drug exposure.

- Glomerulopathy
- Immune thrombocytopenia
- Tumor lysis syndrome (TLS): Patients with significant tumor burden (e.g. bulky metastases) may be at a higher risk. Patients could present with hyperuricemia, hyperphosphatemia, and acute renal failure which may represent possible TLS. Providers should consider additional monitoring and/or treatment as clinically indicated.

7 DRUG INTERACTIONS

Patients who receive anthracycline after stopping PHESGO may be at increased risk of cardiac dysfunction because of PHESGO's long washout period [see Clinical Pharmacology (12.3)]. If possible, avoid anthracycline-based therapy for up to 7 months after stopping PHESGO. If anthracyclines are used, carefully monitor the patient's cardiac function.

8 USE IN SPECIFIC POPULATIONS

8.1 Pregnancy

Pregnancy Pharmacovigilance Program

There is a pregnancy pharmacovigilance program for PHESGO. If PHESGO is administered during pregnancy, or if a patient becomes pregnant while receiving PHESGO or within 7 months following the last dose of PHESGO, health care providers and patients should immediately report PHESGO exposure to Genentech at 1-888-835-2555.

Risk Summary

PHESGO can cause fetal harm when administered to a pregnant woman. In post-marketing reports, use of intravenous trastuzumab during pregnancy resulted in cases of oligohydramnios and oligohydramnios sequence manifesting as pulmonary hypoplasia, skeletal abnormalities, and neonatal death (see Data). In an animal reproduction study, administration of pertuzumab to pregnant cynomolgus monkeys during the period of organogenesis resulted in oligohydramnios, delayed fetal kidney development, and embryo-fetal deaths at clinically relevant exposures that were 2.5 to 20-fold greater than exposures in humans receiving the recommended dose, based on Cmax (see Data). Apprise the patient of the potential risks to a fetus. There are clinical considerations if PHESGO is used during pregnancy or within 7 months prior to conception (see Clinical Considerations).

The estimated background risk of major birth defects and miscarriage for the indicated population is unknown. In the U.S. general population, the estimated background risk of major birth defects and miscarriage in clinically recognized pregnancies is 2-4% and 15-20%, respectively.

Clinical Considerations

Fetal/Neonatal Adverse Reactions

Monitor women who received PHESGO during pregnancy or within 7 months prior to conception for oligohydramnios. If oligohydramnios occurs, perform fetal testing that is appropriate for gestational age and consistent with community standards of care.

Data

Human Data

In post-marketing reports, use of trastuzumab during pregnancy resulted in cases of oligohydramnios and of oligohydramnios sequence, manifesting in the fetus as pulmonary hypoplasia, skeletal abnormalities, and neonatal death. These case reports described oligohydramnios in pregnant women who received trastuzumab either alone or in combination with chemotherapy. In some case reports, amniotic fluid index increased after trastuzumab was stopped. In one case, trastuzumab therapy resumed after amniotic index improved and oligohydramnios recurred.

Animal Data

PHESGO for subcutaneous injection contains pertuzumab, trastuzumab, and hyaluronidase [see Description (11)].

Pertuzumab:

Pregnant cynomolgus monkeys were treated on Gestational Day (GD) 19 with loading doses of 30 to 150 mg/kg pertuzumab, followed by bi-weekly doses of 10 to 100 mg/kg. These dose levels resulted in clinically relevant exposures of 2.5 to 20-fold greater than exposures in humans receiving the recommended dose, based on Cmax. Intravenous administration of pertuzumab from GD19 through GD50 (period of organogenesis) was embryotoxic, with dose-dependent increases in embryo-fetal death between GD25 to GD70. The incidences of embryo-fetal loss were 33, 50, and 85%. At Caesarean section on GD100, oligohydramnios, decreased relative lung and kidney weights, and microscopic evidence of renal hypoplasia consistent with delayed renal development were identified in all pertuzumab dose groups. Pertuzumab exposure was reported in offspring from all treated groups, at levels of 29% to 40% of maternal serum levels at GD100.

Trastuzumab:

In studies where intravenous trastuzumab was administered to pregnant cynomolgus monkeys during the period of organogenesis at doses up to 25 mg/kg given twice weekly (up to 25 times the recommended weekly human dose of 2 mg/kg), trastuzumab crossed the placental barrier during the early (Gestation Days 20 to 50) and late (Gestation Days 120 to 150) phases of gestation. The resulting concentrations of trastuzumab in fetal serum and amniotic fluid were approximately 33% and 25%, respectively, of those present in the maternal serum but were not associated with adverse developmental effects.

Hyaluronidase:

In an embryo-fetal study, mice have been dosed daily by subcutaneous injection during the period of organogenesis with hyaluronidase (recombinant human) at dose levels up to 2,200,000 U/kg, which is >2,400 and 3,600, based on loading and maintenance doses, respectively, times higher than the human dose. The study found no evidence of teratogenicity. Reduced fetal weight and increased numbers of fetal resorptions were observed, with no effects found at a daily dose of 360,000 U/kg, which is >400 and 600, based on loading and maintenance doses, respectively, times higher than the human dose.

In a peri-and post-natal reproduction study, mice have been dosed daily by subcutaneous injection, with hyaluronidase (recombinant human) from implantation through lactation and weaning at dose levels up to 1,100,000 U/kg, which is >1,200 and 1,800, based on loading and maintenance doses, respectively, times higher than the human dose. The study found no adverse effects on sexual maturation, learning and memory or fertility of the offspring.

8.2 Lactation

Risk Summary

There is no information regarding the presence of pertuzumab, trastuzumab or hyaluronidase in human milk, the effects on the breastfed infant, or the effects on milk production. Published data suggest that human IgG is present in human milk but does not enter the neonatal and infant circulation in substantial amounts. Trastuzumab was present in the milk of lactating cynomolgus monkeys but not associated with neonatal toxicity (see Data). Consider the developmental and health benefits of breast feeding along with the mother's clinical need for PHESGO treatment and any potential adverse effects on the breastfed child from PHESGO or from the underlying maternal condition. This consideration should also take into account the elimination half-life of pertuzumab and the trastuzumab wash out period of 7 months [see Clinical Pharmacology (12.3)].

Data

In lactating cynomolgus monkeys, trastuzumab was present in breast milk at about 0.3% of maternal serum concentrations after pre- (beginning Gestation Day 120) and post-partum (through Post-partum Day 28) doses of 25 mg/kg administered twice weekly (25 times the recommended weekly human dose of 2 mg/kg of intravenous trastuzumab). Infant monkeys with detectable serum levels of trastuzumab did not exhibit any adverse effects on growth or development from birth to 1 month of age.

8.3 Females and Males of Reproductive Potential

PHESGO can cause embryo-fetal harm when administered during pregnancy.

Pregnancy Testing

Verify the pregnancy status of females of reproductive potential prior to the initiation of PHESGO.

Contraception

Females

Advise females of reproductive potential to use effective contraception during treatment and for 7 months following the last dose of PHESGO [see Use in Specific Populations (8.1) and Clinical Pharmacology (12.3)].

8.4 Pediatric Use

The safety and effectiveness of PHESGO in pediatric patients have not been established.

8.5 Geriatric Use

Of the total number of patients in the FeDeriCa trial (n=500) treated with PHESGO, 11% were 65 and over, while 1.6% were 75 and over. Clinical studies of PHESGO did not include sufficient numbers of patients age 65 years and older to determine whether they respond differently from younger patients.

In the intravenous trastuzumab trials, the risk of cardiac dysfunction was increased in geriatric patients as compared to younger patients, in both those receiving treatment for adjuvant therapy or metastatic disease. Other differences in safety or effectiveness were not observed between elderly patients and younger patients. In the intravenous pertuzumab in combination with trastuzumab trials, the risk of decreased appetite, anemia, weight decreased, asthenia, dysgeusia, neuropathy peripheral and hypomagnesemia was increased in patients 65 years of age and older compared to patients less than 65 years of age.

11 DESCRIPTION

PHESGO is a combination of pertuzumab, trastuzumab, and hyaluronidase.

Pertuzumab is a recombinant humanized monoclonal antibody that targets the extracellular dimerization domain (Subdomain II) of the human epidermal growth factor receptor 2 protein (HER2). Pertuzumab is produced by recombinant DNA technology in a mammalian cell (Chinese Hamster Ovary) culture. Pertuzumab has an approximate molecular weight of 148 kDa.

Trastuzumab is a humanized IgG1 kappa monoclonal antibody that selectively binds with high affinity to the extracellular domain of the human epidermal growth factor receptor 2 protein, HER2. Trastuzumab is produced by recombinant DNA technology in a mammalian cell (Chinese Hamster Ovary) culture. Trastuzumab has a molecular weight of approximately 148 kDa.

Hyaluronidase (recombinant human) is an endoglycosidase used to increase the dispersion and absorption of co-administered drugs when administered subcutaneously. It is a glycosylated single-chain protein produced by mammalian (Chinese Hamster Ovary) cells containing a DNA plasmid encoding for a soluble fragment of human hyaluronidase (PH20). Hyaluronidase (recombinant human) has a molecular weight of approximately 61 kDa.

PHESGO (pertuzumab, trastuzumab, and hyaluronidase-zzxf) injection is a sterile, preservative-free, clear to opalescent, and colorless to slightly brownish solution supplied in single-dose vials for subcutaneous administration.

PHESGO injection is supplied as two different configurations:

- PHESGO is supplied in a 15 mL single-dose vial containing 1,200 mg of pertuzumab, 600 mg of trastuzumab, and 30,000 units of hyaluronidase, and α,α-trehalose (397 mg), L-histidine (6.75 mg), L-histidine hydrochloric monohydrate (53.7 mg), L-methionine (22.4 mg), polysorbate 20 (6 mg), and sucrose (685 mg) with a pH of 5.5.
- PHESGO is supplied in a 10 mL single-dose vial containing 600 mg of pertuzumab, 600 mg of trastuzumab, and 20,000 units of hyaluronidase, and α,α-trehalose (397 mg), L-histidine (4.4 mg), L-histidine hydrochloric monohydrate (36.1 mg), L-methionine (14.9 mg), polysorbate 20 (4 mg), and sucrose (342 mg) with a pH of 5.5.

12 CLINICAL PHARMACOLOGY

12.1 Mechanism of Action

Pertuzumab targets the extracellular dimerization domain (subdomain II) of HER2 and, thereby, blocks ligand-dependent heterodimerization of HER2 with other HER family members, including EGFR, HER3 and HER4. As a result, pertuzumab inhibits ligand-initiated intracellular signaling through two major signaling pathways, mitogen-activated protein (MAP) kinase and phosphoinositide 3-kinase (PI3K). Inhibition of these signaling pathways can result in cell growth arrest and apoptosis, respectively.

Trastuzumab binds to subdomain IV of the extracellular domain of the HER2 protein to inhibit the ligand-independent, HER2 mediated cell proliferation and PI3K signaling pathway in human tumor cells that overexpress HER2.

Both pertuzumab and trastuzumab-mediated antibody-dependent cell-mediated cytotoxicity (ADCC) have been shown to be preferentially exerted on HER2 overexpressing cancer cells compared with cancer cells that do not overexpress HER2.

While pertuzumab alone inhibited the proliferation of human tumor cells, the combination of pertuzumab and trastuzumab augmented anti-tumor activity in HER2-overexpressing xenograft models.

Hyaluronan is a polysaccharide found in the extracellular matrix of the subcutaneous tissue. It is depolymerized by the naturally occurring enzyme hyaluronidase. Unlike the stable structural components of the interstitial matrix, hyaluronan has a half-life of approximately 0.5 days. Hyaluronidase increases permeability of the subcutaneous tissue by depolymerizing hyaluronan. In the doses administered, hyaluronidase in PHESGO acts transiently and locally.

The effects of hyaluronidase are reversible and permeability of the subcutaneous tissue is restored within 24 to 48 hours.

Hyaluronidase has been shown to increase the absorption rate of a trastuzumab product into the systemic circulation when given in the subcutis of Göttingen Minipigs.

12.2 Pharmacodynamics

The exposure-response relationship and time course of pharmacodynamic response for the safety and effectiveness of pertuzumab and trastuzumab in PHESGO have not been fully characterized.

Cardiac Electrophysiology

The effect of intravenous pertuzumab with an initial dose of 840 mg followed by a maintenance dose of 420 mg every three weeks on QTc interval was evaluated in a subgroup of 20 patients with HER2-positive breast cancer (NCT00567190). No large changes in the mean QT interval (i.e., greater than 20 ms) from placebo based on Fridericia correction method were detected in the trial. A small increase in the mean QTc interval (i.e., less than 10 ms) cannot be excluded because of the limitations of the trial design.

The effects of trastuzumab on electrocardiographic (ECG) endpoints, including QTc interval duration, were evaluated in patients with HER2 positive solid tumors. Trastuzumab had no clinically relevant effect on the QTc interval duration and there was no apparent relationship between serum trastuzumab concentrations and change in QTcF interval duration in patients with HER2 positive solid tumors.

12.3 Pharmacokinetics

The pharmacokinetics (PK) of pertuzumab and trastuzumab were characterized in the FeDeriCa trial following subcutaneous administration of PHESGO (1200 mg pertuzumab/600 mg trastuzumab initial dose followed by 600 mg pertuzumab/600 mg trastuzumab every 3 weeks) and intravenous administration of pertuzumab and trastuzumab (840 mg pertuzumab/8 mg/kg trastuzumab initial dose followed by 420 mg pertuzumab/6 mg/kg trastuzumab every 3 weeks). Trastuzumab is estimated to reach concentrations that are <1 mcg/mL by 7 months in at least 95% patients.

Pertuzumab Cycle 7 Ctrough was 88.7 mcg/mL for PHESGO and 72.4 mcg/mL for intravenous pertuzumab with a geometric mean ratio (GMR) of 1.22 (90% CI: 1.14–1.31). Trastuzumab Cycle 7 Ctrough was 57.5 mcg/mL for PHESGO and 43.2 mcg/mL for intravenous trastuzumab with a GMR of 1.33 (90% CI: 1.24–1.43) [see Clinical Studies (14.2)].

Following subcutaneous administration of PHESGO, the pertuzumab median Cycle 7 Cmax was 34% lower and AUC0-21days was 5% higher than that following intravenous administration of pertuzumab. The median trastuzumab Cycle 7 Cmax was 31% lower and AUC0-21days was 10% higher, than that following intravenous administration of trastuzumab.

Absorption

The mean absolute bioavailability (CV%) was 0.71 (18%) for pertuzumab and 0.77 (13%) for trastuzumab after subcutaneous administration of the approved recommended dosage of PHESGO. The median time to reach Cmax was 3.8 days for both pertuzumab and trastuzumab.

Distribution

The volume of distribution of pertuzumab and trastuzumab at steady state was 2.8 L and 2.9 L, respectively.

Elimination

For pertuzumab, the clearance (CV%) was 0.2 L/day (24%). For trastuzumab, the linear clearance was 0.1 L/day (30%); the non-linear elimination Vmax (CV%) was 12 mg/day (20%) and Km (CV%) was 34 mg/L (39%). The terminal half-life of pertuzumab and trastuzumab was 24 days and 22 days, respectively. Steady state concentration was achieved at Cycle 7 for pertuzumab and at Cycle 11 for trastuzumab.

Specific Populations

No dose adjustments based on body weight or baseline albumin level are needed, as the exposure changes are not considered clinically relevant.

In patients with a body weight <58 kg, mean Cycle 7 AUC0-21 days of trastuzumab was about 33% higher after PHESGO than after intravenous trastuzumab treatment, whereas in the highest BW group (>77 kg) Cycle 7 AUC0-21 days was 24% lower after PHESGO than after intravenous trastuzumab treatment. However, no body weight-based dose adjustments are needed, as the exposure changes are not considered clinically relevant.

No clinically significant differences in the pharmacokinetics of pertuzumab and trastuzumab were observed based on age (25 to 80 years), race (Asian and non-Asian), and renal impairment (creatinine clearance 30 mL/min or greater determined by Cockcroft-Gault). The effects of hepatic impairment on the pharmacokinetics of pertuzumab and trastuzumab are unknown.

Drug Interaction Studies

There have been no formal clinical drug interaction studies performed with PHESGO.

12.6 Immunogenicity

The observed incidence of anti-drug antibodies (ADA) is highly dependent on the sensitivity and specificity of the assay. Differences in assay methods preclude meaningful comparisons of the incidence of ADA in the trial described below, including those of PHESGO or of other pertuzumab or trastuzumab products.

During treatment and post-treatment with subcutaneous administration of PHESGO and concurrent administration with neoadjuvant chemotherapy in the FeDeriCa trial [see Clinical Studies (14.1)], the incidence of anti-pertuzumab and anti-trastuzumab antibodies was 12.9% (31/241) and 2.1% (5/241), respectively. During treatment and post-treatment with intravenous pertuzumab and trastuzumab and concurrent administration with neoadjuvant chemotherapy, the incidence of anti-pertuzumab and anti-trastuzumab antibodies was 10.6 % (26/245) and 0.4% (1/245), respectively. The incidence of neutralizing antibodies (NAb) to pertuzumab and to trastuzumab was 6% (2/31) and 20% (1/5), respectively, in patients treated with PHESGO. The corresponding incidences of NAb were 11.5% (3/26) and 0% (0/1), respectively, in patients treated with intravenous pertuzumab and trastuzumab. Because of limited immunogenicity data, the effect of anti-pertuzumab and anti-trastuzumab antibodies on the pharmacokinetics and effectiveness of PHESGO is unknown. There was no identified clinically significant effect of anti-pertuzumab and anti-trastuzumab antibodies on the safety of PHESGO.

In the FeDeriCa trial, the incidence of anti-rHuPH20 antibodies was 6.3% (15/238) and the incidence of NAb was 0% (0/15) in patients treated with PHESGO. Because of limited immunogenicity data, the clinical impact of anti-rHuPH20 antibodies is unknown.

13 NONCLINICAL TOXICOLOGY

13.1 Carcinogenesis, Mutagenesis, Impairment of Fertility

PHESGO contains pertuzumab, trastuzumab, and hyaluronidase.

Pertuzumab

Studies have not been performed to evaluate the carcinogenicity or mutagenic potential of pertuzumab. No specific fertility studies in animals have been performed to evaluate the effect of pertuzumab.

No adverse effects on male and female reproductive organs were observed in repeat-dose toxicity studies of up to six months duration in cynomolgus monkeys.

Trastuzumab

Trastuzumab has not been tested for carcinogenicity potential.

No evidence of mutagenic activity was observed when trastuzumab was tested in the standard Ames bacterial and human peripheral blood lymphocyte mutagenicity assays at concentrations of up to 5000 mcg/mL. In an in vivo micronucleus assay, no evidence of chromosomal damage to mouse bone marrow cells was observed following bolus intravenous doses of up to 118 mg/kg of trastuzumab.

A fertility study was conducted in female cynomolgus monkeys at doses up to 25 times the weekly recommended human dose of 2 mg/kg of intravenous trastuzumab and has revealed no evidence of impaired fertility, as measured by menstrual cycle duration and female sex hormone levels.

Hyaluronidase

Hyaluronidases are found in most tissues of the body. Long-term animal studies have not been performed to assess the carcinogenic or mutagenic potential of hyaluronidase. In addition, when subcutaneous hyaluronidase (recombinant human) was administered to cynomolgus monkeys for 39 weeks at dose levels up to 220,000 U/kg, which is >223 and 335, based on loading and maintenance doses, respectively, times higher than the human dose, no evidence of toxicity to the male or female reproductive system was found through periodic monitoring of in-life parameters, e.g., semen analyses, hormone levels, menstrual cycles, and also from gross pathology, histopathology and organ weight data.

14 CLINICAL STUDIES

14.1 Neoadjuvant and Adjuvant Treatment of Breast Cancer

The effectiveness of PHESGO for use in combination with chemotherapy has been established for the treatment of patients with HER2-positive early breast cancer. Use of PHESGO for this indication is supported by evidence from adequate and well-controlled studies conducted with intravenous pertuzumab and intravenous trastuzumab administered in combination with chemotherapy in adults with HER2-overexpressing early breast cancer (NCT00545688, NCT00976989, NCT02132949, NCT01358877) and additional pharmacokinetic and safety data that demonstrated comparable pharmacokinetics and safety profiles between PHESGO and intravenous pertuzumab and intravenous trastuzumab in FeDeriCa [see Adverse Reactions (6.1) and Clinical Pharmacology (12.3)].

FeDeriCa

The FeDeriCa trial (NCT03493854) was an open-label, multicenter, randomized trial conducted in 500 patients with operable or locally advanced (including inflammatory) HER2-positive breast cancer with a tumor size >2 cm or node-positive. HER2 overexpression was defined as IHC 3+ in >10% of immunoreactive cells or HER2 gene amplification by ISH (ratio of HER2 gene signals to centromere 17 signals ≥2.0) using an FDA-approved test. Patients were randomized to receive 8 cycles of neoadjuvant chemotherapy with concurrent administration of 4 cycles of either PHESGO or intravenous pertuzumab and trastuzumab during cycles 5-8, followed by surgery. Investigators selected one of two of the following neoadjuvant chemotherapy regimens for individual patients:

- 4 cycles of doxorubicin (60 mg/m^2) and cyclophosphamide (600 mg/m^2) every 2 weeks followed by paclitaxel (80 mg/m^2) weekly for 12 weeks
- 4 cycles of doxorubicin (60 mg/m^2) and cyclophosphamide (600 mg/m^2) every 3 weeks followed by 4 cycles of docetaxel (75 mg/m^2 for the first cycle and then 100 mg/m^2 at subsequent cycles at the investigator's discretion) every 3 weeks

Following surgery, patients continued therapy with PHESGO or intravenous pertuzumab and trastuzumab as treated prior to surgery, for an additional 14 cycles, to complete 18 cycles of anti-HER2 therapy. Patients also received adjuvant radiotherapy and endocrine therapy as per investigator's discretion. In adjuvant period, substitution of intravenous trastuzumab for subcutaneous trastuzumab was permitted at investigator discretion. Patients received HER2-targeted therapy every 3 weeks according to Table 5 as follows:

Table 5: Dosing and Administration of PHESGO, Intravenous Pertuzumab, Intravenous Trastuzumab, and Subcutaneous Trastuzumab
Medication | Administration | Dose
Medication | Administration | Initial | Maintenance
PHESGO | Subcutaneously | 1200 mg/600 mg | 600mg/600 mg
Pertuzumab | Intravenously | 840 mg | 420 mg
Trastuzumab | Intravenously | 8 mg/kg | 6 mg/kg
Trastuzumab-oysk | Subcutaneously [In adjuvant period substitution of intravenous trastuzumab for subcutaneous trastuzumab was permitted at investigator discretion] | 600 mg

FeDeriCa was designed to demonstrate non-inferiority of the Cycle 7 (i.e., pre-dose Cycle 8) pertuzumab serum Ctrough from PHESGO pertuzumab to the intravenous pertuzumab (major efficacy outcome measure) [see Clinical Pharmacology 12.3]. Additional outcome measures included Cycle 7 serum trastuzumab Ctrough, efficacy (pathological complete response [pCR], defined as the absence of invasive neoplastic cells in the breast and in the axillary lymph nodes), and safety.

The median age of patients was 51 years (range: 25-81); 99% were female; 66% were White, 21% were Asian, 4% were American Indian or Alaska Native, 1.2% were Black or African American, 15% were Hispanic or Latino. The majority of patients had hormone receptor-positive disease (61%) or node-positive disease (58%).

Table 6: Summary of Pathological Complete Response (pCR) (FeDeriCa)
 | PHESGO n=248 | Intravenous pertuzumab + trastuzumab n=252
pCR: ypT0/is, ypN0 | 148 (59.7%) | 150 (59.5%)
Exact 95% CI for pCR Rate [Confidence interval for one sample binomial using Pearson-Clopper method] | (53.3%, 65.8%) | (53.2%, 65.6%)
Difference in pCR rate (SC minus IV arm) | 0.15%
95% CI for the difference in pCR [Hauck-Anderson continuity correction has been used in this calculation] rate | (-8.7%; 9.0%)

14.2 Metastatic Breast Cancer

The effectiveness of PHESGO for use in combination with docetaxel has been established for the treatment of patients with HER2-positive metastatic breast cancer who have not received prior anti-HER2 therapy or chemotherapy for metastatic disease. Use of PHESGO for this indication is supported by evidence from adequate and well-controlled studies conducted with intravenous pertuzumab and intravenous trastuzumab administered in combination with chemotherapy in adults with HER2-overexpressing metastatic breast cancer (NCT00567190) and additional pharmacokinetic and safety data that demonstrated comparable pharmacokinetics and safety profiles between PHESGO and intravenous pertuzumab and intravenous trastuzumab in FeDeriCa [see Adverse Reactions (6.1), Clinical Pharmacology (12.3), and Clinical Studies (14.2)].

14.3 Patient Experience

The PHranceSCa trial (NCT03674112) was a randomized, multi-center, open-label cross-over trial conducted in 160 patients with HER2-positive breast cancer undergoing adjuvant treatment. All patients completed neoadjuvant treatment with pertuzumab, trastuzumab and chemotherapy and had surgery before randomization. Following randomization, 80 patients in arm A received 3 cycles of intravenous pertuzumab and trastuzumab followed by 3 cycles of PHESGO and 80 patients in arm B received 3 cycles of PHESGO followed by 3 cycles of intravenous pertuzumab and trastuzumab. All patients received 18 total cycles of HER2-targeted therapy. After Cycle 6, 136 out of 160 patients (85%) reported preferring subcutaneous administration of PHESGO over intravenous pertuzumab and trastuzumab and the most common reason was that administration required less time in the clinic. After Cycle 6, 22 out of 160 patients (14%) reported preferring intravenous pertuzumab and trastuzumab over PHESGO and the most common reason was feels more comfortable during administration. Two out of 160 patients (1%) had no preference for the route of administration. All 160 patients (100%) completed the preference questionnaire.

16 HOW SUPPLIED/STORAGE AND HANDLING

How Supplied

PHESGO (pertuzumab, trastuzumab, and hyaluronidase-zzxf) injection is a sterile, preservative-free, clear to opalescent, and colorless to slightly brownish solution in single-dose vials for subcutaneous administration supplied as each carton containing one single-dose vial:

- 1,200 mg pertuzumab, 600 mg trastuzumab, and 30,000 units hyaluronidase/15 mL (80 mg, 40 mg, and 2,000 units/mL) (NDC 50242-245-01).
- 600 mg pertuzumab, 600 mg trastuzumab, and 20,000 units hyaluronidase/10 mL (60 mg, 60 mg, 2,000 units/mL) (NDC 50242-260-01).

Storage and Handling

Store PHESGO vials in the refrigerator at 2°C to 8°C (36°F to 46°F) in the original carton to protect from light.

Do not freeze. Do not shake.

17 PATIENT COUNSELING INFORMATION

Cardiomyopathy

- Advise patients to contact a health care professional immediately for any of the following: new onset or worsening shortness of breath, cough, swelling of the ankles/legs, swelling of the face, palpitations, weight gain of more than 5 pounds in 24 hours, dizziness or loss of consciousness [see Warnings and Precautions (5.1)].

Embryo-Fetal Toxicity

- Advise pregnant women and females of reproductive potential that exposure to PHESGO during pregnancy or within 7 months prior to conception can result in fetal harm. Advise female patients to contact their healthcare provider with a known or suspected pregnancy [see Use in Specific Populations (8.1)].
- Advise women who are exposed to PHESGO during pregnancy or within 7 months prior to conception that there is a pregnancy pharmacovigilance program that monitors pregnancy outcomes. Encourage these patients to report their pregnancy to Genentech [see Use in Specific Populations (8.1)].
- Advise females of reproductive potential to use effective contraception during treatment and for 7 months following the last dose of PHESGO [see Use in Specific Populations (8.3)].

Hypersensitivity and Administration-Related Reactions

- Advise patients to contact their healthcare provider immediately and to report any symptoms of hypersensitivity and administration-related reactions including dizziness, nausea, chills, fever, vomiting, diarrhea, urticaria, angioedema, breathing problems, or chest pain [see Warnings and Precautions (5.5)].

PHESGO® [pertuzumab, trastuzumab, and hyaluronidase-zzxf]

Manufactured by:
Genentech, Inc.
A Member of the Roche Group
1 DNA Way
South San Francisco, CA 94080-4990

U.S. License No.: 1048

PHESGO® is a trademark of Genentech, Inc.
©2024 Genentech, Inc.

Representative sample of labeling (see the HOW SUPPLIED section for complete listing):

PRINCIPAL DISPLAY PANEL - 15 mL Vial Carton

NDC 50242-245-01
Phesgo®
(pertuzumab, trastuzumab,
and hyaluronidase-zzxf)
Injection

1,200 mg, 600 mg, and
30,000 units/15 mL
(80 mg, 40 mg, and 2,000 units/mL)

For subcutaneous injection
over 8 minutes
Single-Dose Vial
Discard Unused Portion

1 vial
Rx only
Genentech
11021888

PRINCIPAL DISPLAY PANEL - 10 mL Vial Carton

NDC 50242-260-01
Phesgo®
(pertuzumab, trastuzumab,
and hyaluronidase-zzxf)
Injection

600 mg, 600 mg, and
20,000 units/10 mL
(60 mg, 60 mg, and 2,000 units/mL)

For subcutaneous injection
over 5 minutes
Single-Dose Vial
Discard Unused Portion

1 vial
Rx only
Genentech
11021892